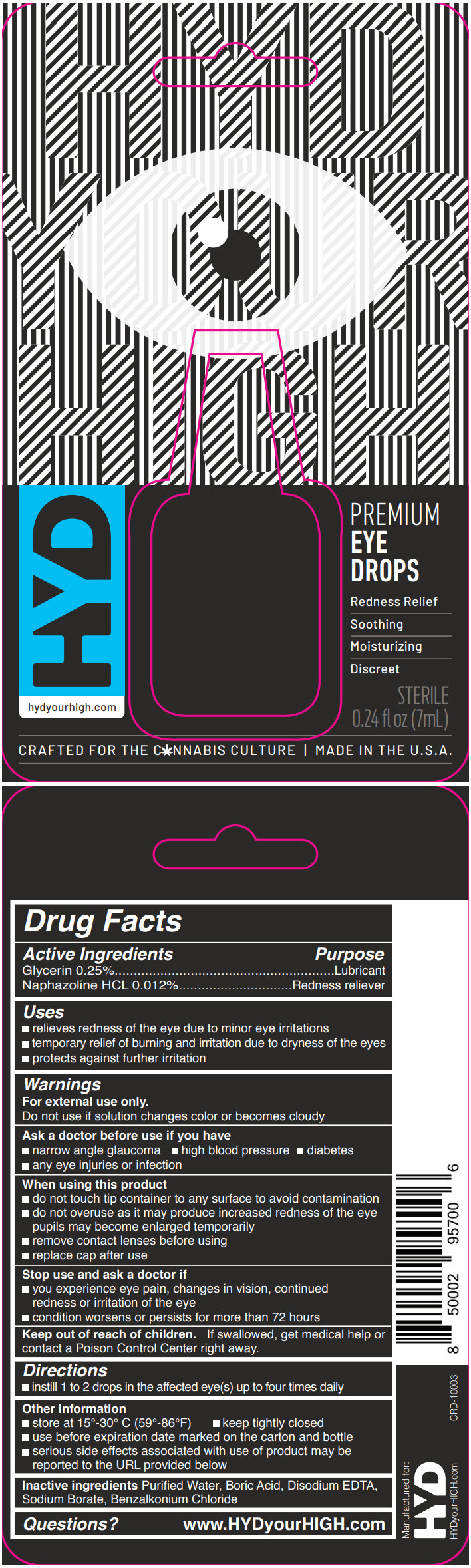 DRUG LABEL: HYD
NDC: 72632-001 | Form: SOLUTION/ DROPS
Manufacturer: HyConcepts
Category: otc | Type: HUMAN OTC DRUG LABEL
Date: 20181112

ACTIVE INGREDIENTS: Glycerin 2.5 mg/1 mL; Naphazoline Hydrochloride 0.12 mg/1 mL
INACTIVE INGREDIENTS: Water; Boric Acid; Edetate Disodium Anhydrous; Sodium Borate; Benzalkonium Chloride

HYD

Drug Facts

ACTIVE INGREDIENT

Active Ingredients | Purpose
Glycerin 0.25% | Lubricant
Naphazoline HCL 0.012% | Redness reliever

Uses

- relieves redness of the eye due to minor eye irritations
- temporary relief of burning and irritation due to dryness of the eyes
- protects against further irritation

Warnings

For external use only.

Do not use if solution changes color or becomes cloudy

Ask a doctor before use if you have

- narrow angle glaucoma
- high blood pressure
- diabetes
- any eye injuries or infection

When using this product

- do not touch tip container to any surface to avoid contamination
- do not overuse as it may produce increased redness of the eye pupils may become enlarged temporarily
- remove contact lenses before using
- replace cap after use

Stop use and ask a doctor if

- you experience eye pain, changes in vision, continued redness or irritation of the eye
- condition worsens or persists for more than 72 hours

Keep out of reach of children. If swallowed, get medical help or contact a Poison Control Center right away.

Directions

- instill 1 to 2 drops in the affected eye(s) up to four times daily

Other information

- store at 15°-30° C (59°-86°F)
- keep tightly closed
- use before expiration date marked on the carton and bottle
- serious side effects associated with use of product may be reported to the URL provided below

Inactive ingredients

Purified Water, Boric Acid, Disodium EDTA, Sodium Borate, Benzalkonium Chloride

Questions?

www.HYDyourHIGH.com

PRINCIPAL DISPLAY PANEL - 7 mL Bottle Blister Pack

HYD
YOUR
HIGH

HYD
hydyourhigh.com

PREMIUM
EYE
DROPS

Redness Relief
Soothing
Moisturizing
Discreet

STERILE
0.24 fl oz (7mL)

CRAFTED FOR THE CANNABIS CULTURE | MADE IN THE U.S.A.